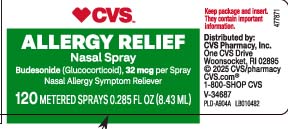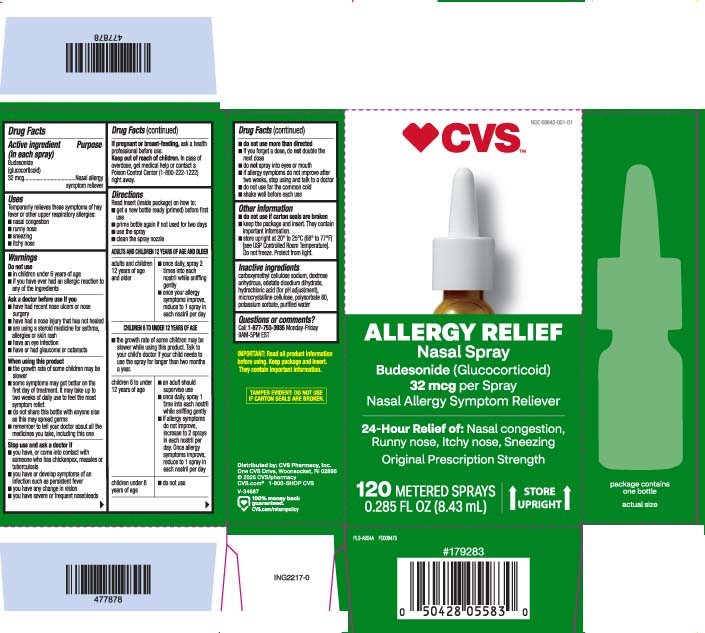 DRUG LABEL: Budesonide
NDC: 69842-001 | Form: SPRAY, METERED
Manufacturer: CVS Pharmacy
Category: otc | Type: HUMAN OTC DRUG LABEL
Date: 20260121

ACTIVE INGREDIENTS: BUDESONIDE 32 ug/1 1
INACTIVE INGREDIENTS: EDETATE DISODIUM; CARBOXYMETHYLCELLULOSE SODIUM, UNSPECIFIED; MICROCRYSTALLINE CELLULOSE; DEXTROSE, UNSPECIFIED FORM; POTASSIUM SORBATE; POLYSORBATE 80; HYDROCHLORIC ACID; WATER

Drug Facts

Active ingredient (in each spray)

Budesonide (glucocorticoid) 32 mcg

Purpose

Nasal allergy symptom reliever

Uses

Temporarily relieves these symptoms of hay fever or other upper respiratory allergies:

- nasal congestion
- runny nose
- itchy nose
- sneezing

Warnings

Do not use

- in children under 6 years of age
- if you have ever had an allergic reaction to any of the ingredients

Ask a doctor before use if you

- have had recent nose ulcers or nose surgery
- have had a nose injury that has not healed
- are using a steroid medicine for asthma, allergies or skin rash
- have an eye infection
- have or had glaucoma or cataracts

When using this product

- the growth rate of some children may be slower
- some symptoms may get better on the first day of treatment. It may take up to two weeks of daily use to feel the most symptom relief.
- do not share this bottle with anyone else as this may spread germs
- remember to tell your doctor about all the medicines you take, including this one

Stop use and ask a doctor if

- you have, or come into contact with someone who has, chickenpox, measles or tuberculosis
- you have or develop symptoms of an infection such as persistent fever
- you have any change in vision
- you have severe or frequent nosebleeds

If pregnant or breast-feeding,

ask a health professional before use.

Keep out of reach of children.

In case of overdose, get medical help or contact a Poison Control Center (1-800-222-1222) right away.

Direction

Read insert (inside package) on how to:

- get a new bottle ready (primed) before first use
- prime bottle again if not used for two days
- use the spray
- clean the spray nozzle

ADULTS AND CHILDREN 12 YEARS OF AGE AND OLDER

Adults and children 12 years of age and older | - once daily, spray 2 times into each nostril while sniffing gently - once your allergy symptoms improve, reduce to 1 spray in each nostril per day

CHILDREN 6 TO UNDER 12 YEARS OF AGE

- the growth rate of some children may be slower while using this product. Talk to your child's doctor if yours child needs to use the spray for longer than two months a year

children 6 to under 12 years of age | - an adult should supervise use - once daily, spray 1 times into each nostril while sniffing gently - if allergy symptoms do not improve, increase to 2 sprays in each nostril per day. Once allergy symptoms improve, reduce to 1 spray in each nostril per day
children under 6 years of age | - do not use

- do not use more than directed
- if you forget a dose, do not double the next dose
- do not spray into eyes or mouth
- if allergy symptoms do not improve after two weeks, stop using and talk to a doctor
- do not use for the common cold
- shake well before each use

Other information

- do not use if carton is seal are broken
- keep the package and insert. They contain important information.
- store upright at 20° to 25°C (68° to 77°F) [see USP Controlled Room Temperature]. Do not freeze. Protect from light.

Inactive ingredients

carboxymethyl cellulose sodium, dextrose anhydrous, edetate disodium dihydrate, hydrochloric acid (for pH adjustment), microcrystalline cellulose, polysorbate 80, potassium sorbate, purified water

Questions or comments?

call 1-877-753-3935 Monday-Friday 9AM-5PM EST

Principal Display Panel

ALLERGY RELIEF

Nasal Spray

bedesonide (Glucocorticoid) 32 mcg per Spray

24-Hour Relief of: Nasal congestion, Runny nose, Itchy nose, Sneezing

Original Prescription Strength

STORE UPRIGHT

METERED SPRAYS

FL OZ (mL)

IMPORTANT: Read all product information before using. Keep package and insert. They contain important information.

TAMPER EVIDENT: DO NOT USE IF CARTON SEALS ARE BROKEN.

Distributed by: CVS Pharmacy, Inc.

One CVS Drive, Woonsocket, RI 02895

Package label

CVS Nasal Spray
CVS Allergy Relief